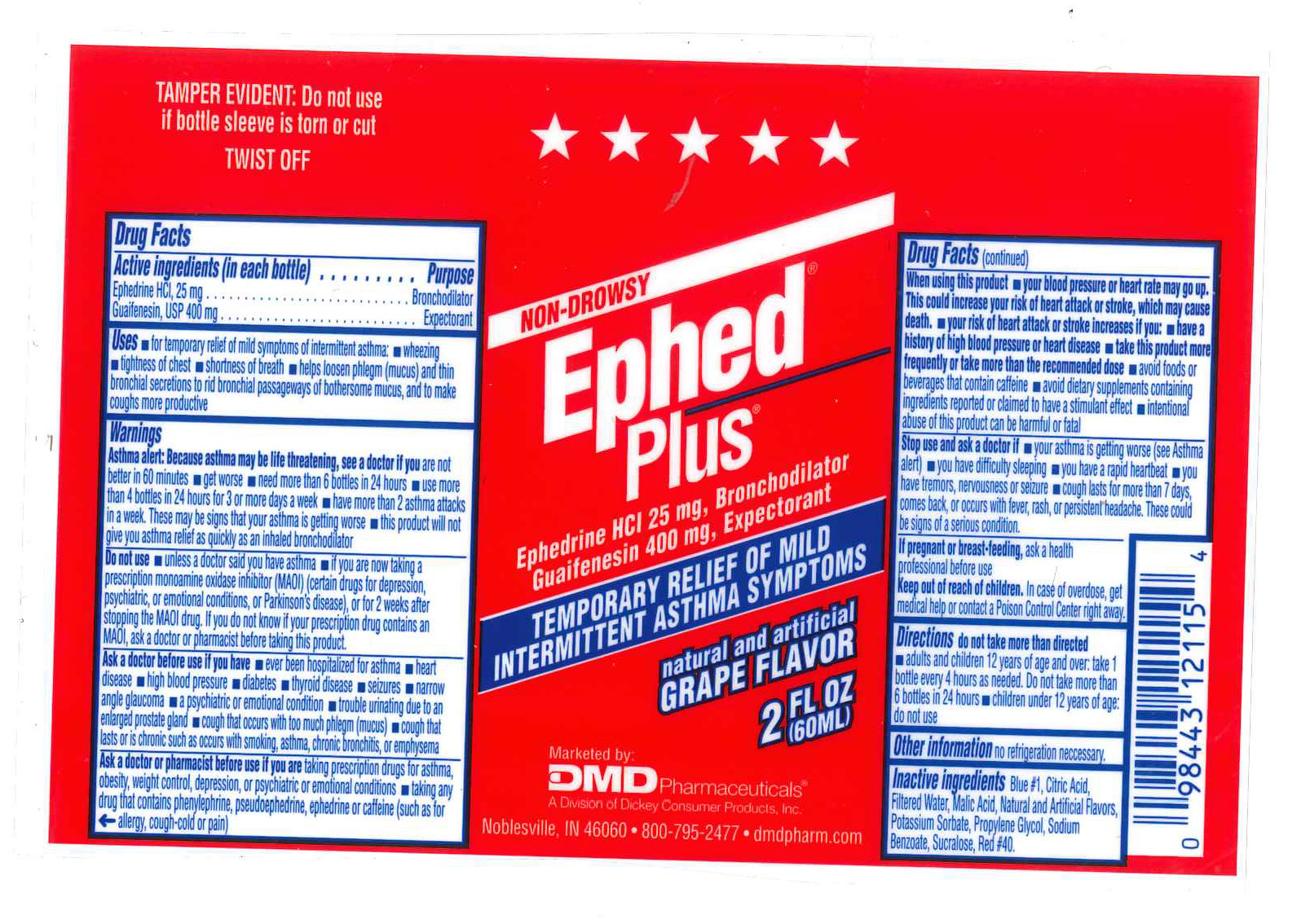 DRUG LABEL: Ephed Plus Liquid
NDC: 65193-180 | Form: LIQUID
Manufacturer: Dickey Consumer Products DBA DMD
Category: otc | Type: HUMAN OTC DRUG LABEL
Date: 20190402

ACTIVE INGREDIENTS: EPHEDRINE HYDROCHLORIDE 25 mg/60 mL; guaifenesin 400 mg/60 mL
INACTIVE INGREDIENTS: WATER; FD&C BLUE NO. 1; FD&C RED NO. 40; POTASSIUM SORBATE; SODIUM BENZOATE; SUCRALOSE; CITRIC ACID MONOHYDRATE; MALIC ACID; PROPYLENE GLYCOL

Drug Facts

Warnings

Purpose: Bronchodilator, Expectorant

INDICATIONS AND USAGE

Uses for temporary relief of mild symptoms of intermittent asthma: wheezing
tightness of chest , shortness of breath , helps loosen phlegm (mucus) and thin
bronchial secretions to rid bronchial passageways of bothersome mucus, and to make
coughs more productive

Keep out of reach of children. In case of overdose, get
medical help or contact a Poison Control Center right away.

If pregnant or breast-feeding, ask a health
professional before use

DOSAGE AND ADMINISTRATION

Directions do not take more than directed

adults and children 12 years of age and over: take 1

bottle every 4 hours as needed. Do not take more than

6 bottles in 24 hours children under 12 years of age:

do not use

Inactive ingredients Blue #1, Citric Acid,
Filtered Water, Malic Acid, Natural and Artificial Flavors,
Potassium Sorbate, Propylene Glycol, Sodium

ACTIVE INGREDIENT

Ephedrine HCI 25 mg, Bronchodilator
Guaifenesin 400 mg, Expectorant